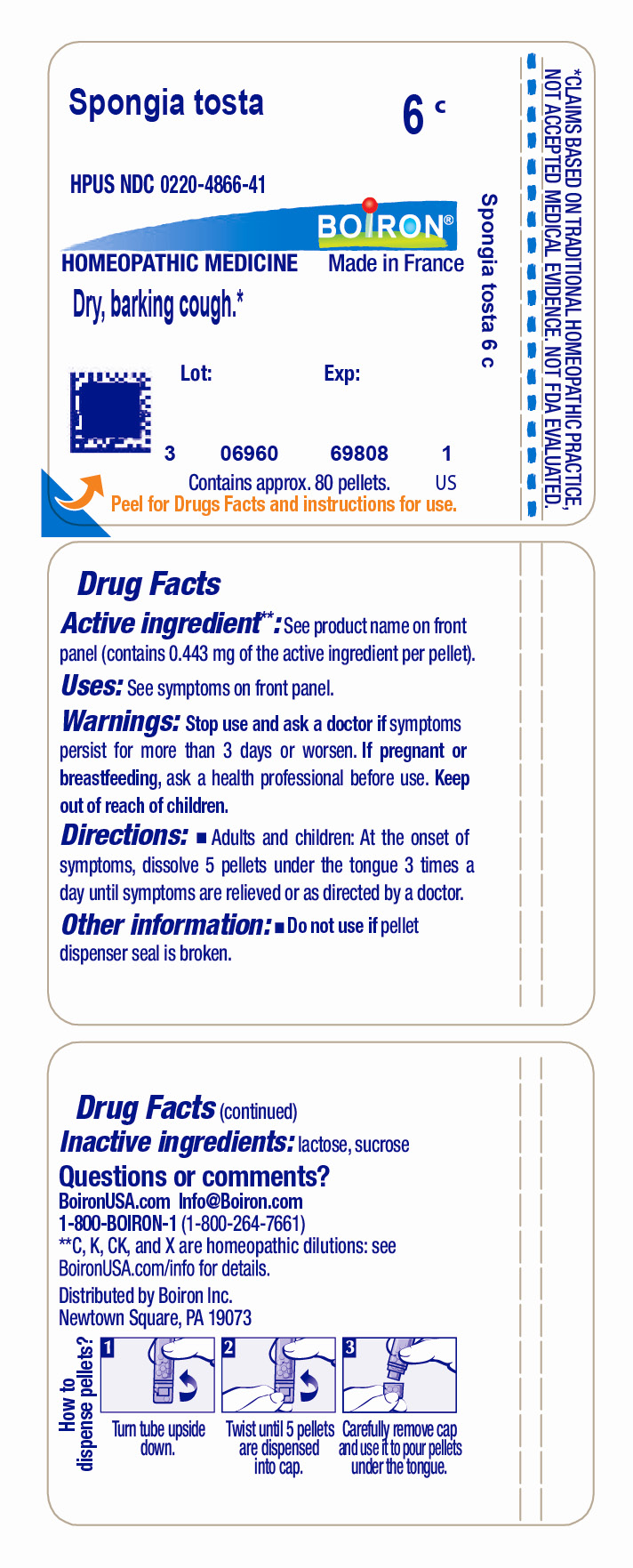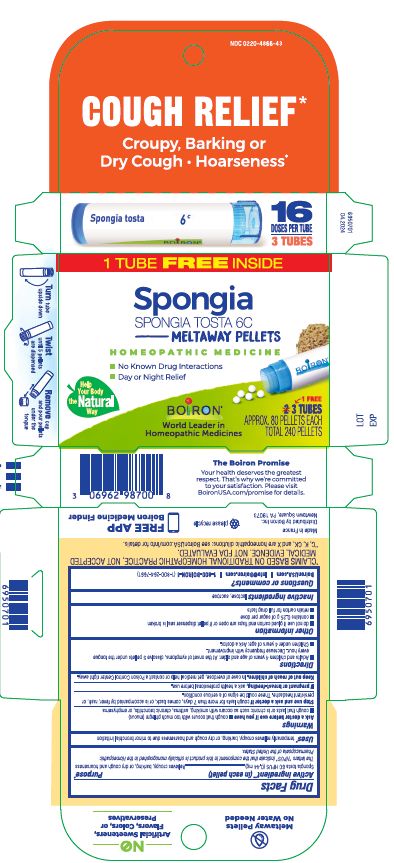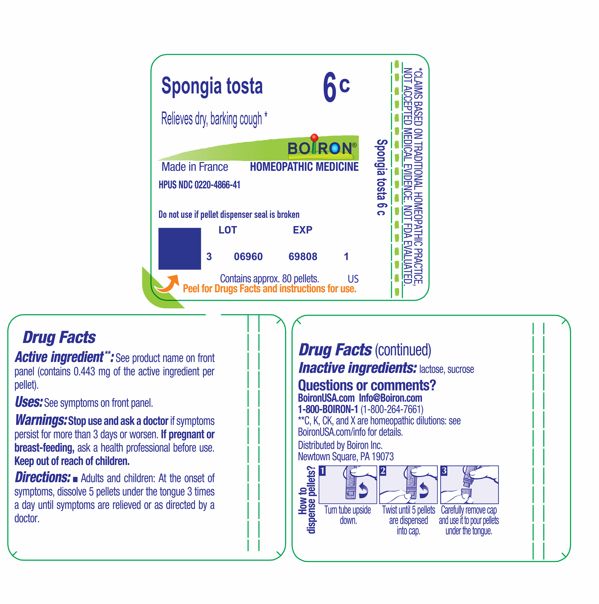 DRUG LABEL: Spongia tosta
NDC: 0220-4866 | Form: PELLET
Manufacturer: Boiron
Category: homeopathic | Type: HUMAN OTC DRUG LABEL
Date: 20240625

ACTIVE INGREDIENTS: SPONGIA OFFICINALIS SKELETON, ROASTED 6 [hp_C]/6 [hp_C]
INACTIVE INGREDIENTS: LACTOSE, UNSPECIFIED FORM; SUCROSE

Spongia tosta 6C

Active ingredient ** (in each pellet)

Spongia tosta 6C HPUS

(**contains 0.443 mg of the active ingredient per pellet)

The letters "HPUS" indicate that the components in this product are officially monographed in the Homeopathic Pharmacopoeia of the United States.

PURPOSE

Relieves croupy, barking, or dry cough and hoarseness*

INDICATIONS AND USAGE

Cough Relief Uses*

temporarily relieves croupy, barking, or dry cough and hoarseness due to minor bronchial irritation

Tube Uses*

Relieves dry, barking cough *

WARNINGS

Cough Relief Carton

Ask a doctor before use if you have

- cough that occurs with too much phlegm (mucus)
- cough that lasts or is chronic such as occurs with smoking, asthma, chronic bronchitis, or emphysema

STOP USE

Cough Relief Carton

Stop use and ask a doctor if cough lasts more than 7 days, comes back, or is accompanied by fever, rash, or persistent headache. These could be signs of a serious condition.

Tube

Stop use and ask a doctor if symptoms persist for more than 3 days or worsen.

PREGNANCY OR BREAST FEEDING

If pregnant or breast-feeding, ask a health professional before use.

Keep out of reach of children. In case of accidental overdose, get medical help or contact a Poison Control Center right away.

DOSAGE AND ADMINISTRATION

Cough Relief Carton

Adults and children 4 years of age and older: At the onset of symptoms, dissolve 5 pellets under the tongue every hour. Decrease frequency with improvement.
Children under 4 years of age: Ask a doctor.

Tube

Adults and children: At the onset of symptoms, dissolve 5 pellets under the tongue 3 times a day until symptoms are relieved or as directed by a doctor.

INACTIVE INGREDIENT

lactose, sucrose

Cough Relief Carton

Cough Relief*

Croupy, Barking or Dry Cough Hoarseness

3 Tubes

Approx 80 pellets each

16 Doses per tube

Total 240 pellets

do not use if glued carton end flaps are open or if pellet dispenser seal is broken

contains 0.25 g of sugar per dose

Turn tube upside down. Twist until 5 pellets are dispensed. Remove the cap and use it to pour pellets under tongue.

Tube

Do not use if pellet dispenser seal is broken.
Contains approx 80 pellets.
How to dispense pellets? Turn tube upside down. Twist until 5 pellets are dispensed into cap. Carefully remove the cap and use it to pour pellets under the tongue.

*CLAIMS BASED ON TRADITIONAL HOMEOPATHIC PRACTICE NOT ACCEPTED MEDICAL EVIDENCE. NOT FDA EVALUATED.
*C,K,CK, and X are homeopathic dilutions: see BoironUSA.com/info for details.

QUESTIONS

BoironUSA.com Info@boiron.com
1-800-BOIRON-1 (1-800-264-7661)
Distributed by Boiron, Inc.
Newtown Square, PA 19073